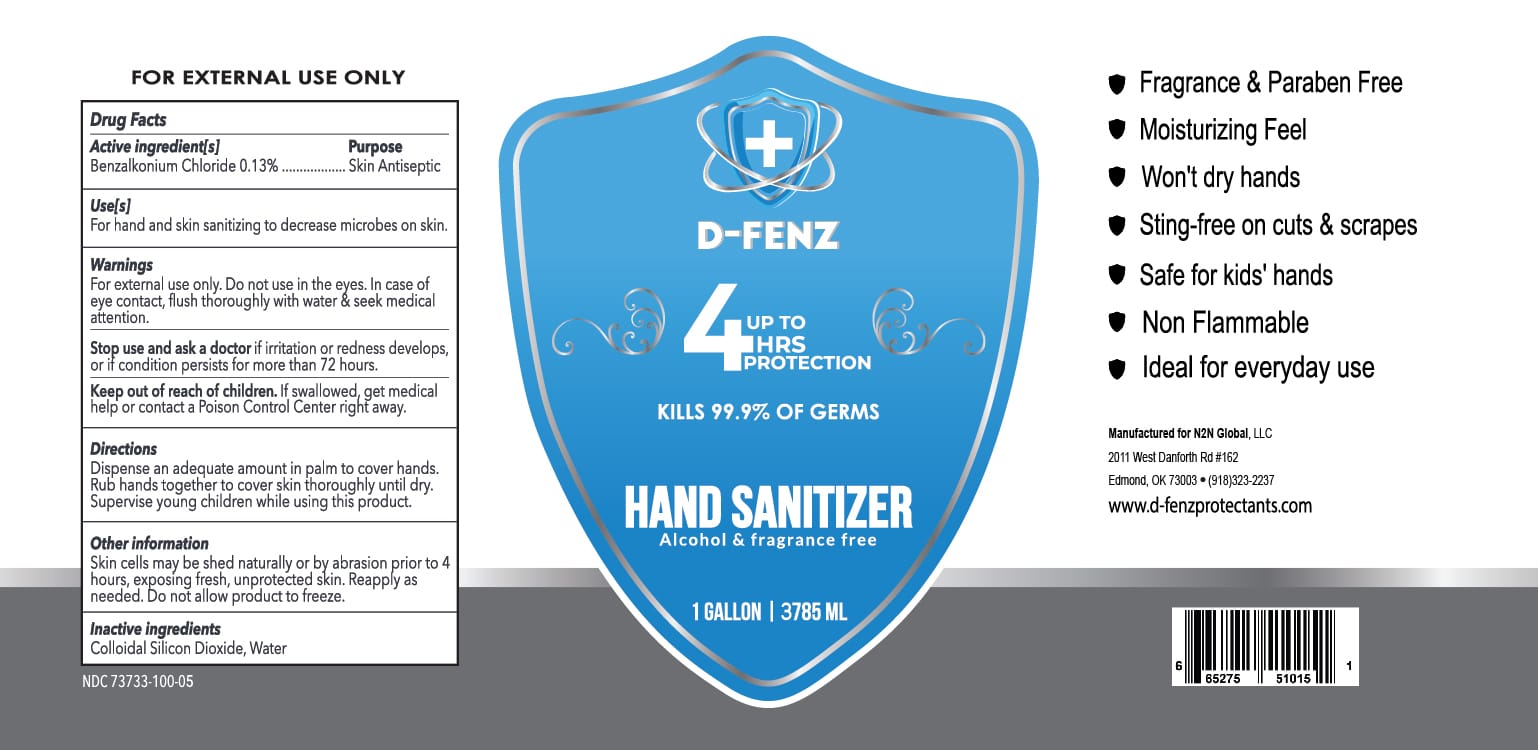 DRUG LABEL: D-FENZ Hand Sanitizer
NDC: 73733-100 | Form: LIQUID
Manufacturer: N2N Global, LLC
Category: otc | Type: HUMAN OTC DRUG LABEL
Date: 20220714

ACTIVE INGREDIENTS: BENZALKONIUM CHLORIDE 0.13 g/100 mL
INACTIVE INGREDIENTS: SILICON DIOXIDE 0.2 g/100 mL; WATER 99.67 g/100 mL

D-FENZ Hand Sanitizer

Active Ingredients

Benzalkonium Chloride 0.13%

Purpose

Skin Antiseptic

Uses

For hand and skin sanitizing to decrease microbes on skin

Warnings

For external use only. Do not use in the eyes. In case of eye contact, flush thoroughly with water & seek medical attention.

Stop use and ask a doctor if irritation or redness develops, or if condition persists for more than 72 hours.

Keep out of reach of children

If swallowed, get medical help or contact a Poison Control Center right away.

Directions

Dispense an adequate amount in palm to cover hands. Rub hands together to cover skin thoroughly until dry. Supervise young children while using this product.

Other Information

Skin cells may be shed naturally or by abrasion prior to 4 hours, exposing fresh, unprotected skin. Reapply as needed.

Inactive Ingredients

Colloidal Silicon Dioxide

Questions?

inquiries@N2Ncleangreen.com

www.n2ncleangreen.com

N2N Global, LLC

2011 West Danforth Rd #162

Edmond, OK 73003